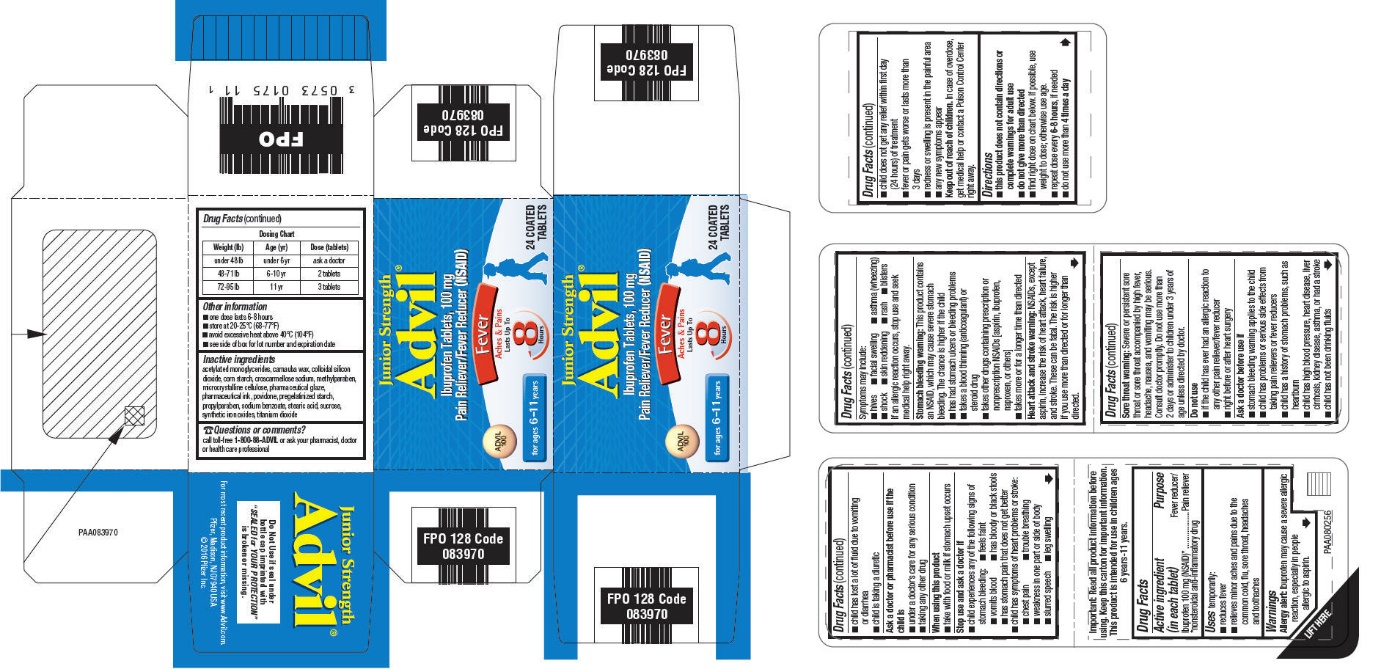 DRUG LABEL: JUNIOR STRENGTH ADVIL
NDC: 0573-0175 | Form: TABLET, COATED
Manufacturer: Haleon US Holdings LLC
Category: otc | Type: HUMAN OTC DRUG LABEL
Date: 20240422

ACTIVE INGREDIENTS: IBUPROFEN 100 mg/1 1
INACTIVE INGREDIENTS: DIACETYLATED MONOGLYCERIDES; CARNAUBA WAX; SILICON DIOXIDE; STARCH, CORN; CROSCARMELLOSE SODIUM; METHYLPARABEN; MICROCRYSTALLINE CELLULOSE; SHELLAC; POVIDONE, UNSPECIFIED; PROPYLPARABEN; SODIUM BENZOATE; STEARIC ACID; SUCROSE; FERRIC OXIDE RED; TITANIUM DIOXIDE

Drug Facts

ACTIVE INGREDIENT (IN EACH TABLET)

Ibuprofen 100 mg (NSAID)*

*nonsteroidal anti-inflammatory drug

PURPOSE

Fever reducer/Pain reliever

USES

temporarily:

- reduces fever
- relieves minor aches and pains due to the common cold, flu, sore throat, headaches and toothaches

WARNINGS

Allergy alert:

Ibuprofen may cause a severe allergic reaction, especially in people allergic to aspirin. Symptoms may include:

- hives
- facial swelling
- asthma (wheezing)
- shock
- skin reddening
- rash
- blisters

If an allergic reaction occurs, stop use and seek medical help right away.

Stomach bleeding warning:

This product contains an NSAID, which may cause severe stomach bleeding. The chance is higher if the child

- has had stomach ulcers or bleeding problems
- takes a blood thinning (anticoagulant) or steroid drug
- takes other drugs containing prescription or nonprescription NSAIDs [aspirin, ibuprofen, naproxen, or others]
- takes more or for a longer time than directed

Heart attack and stroke warning

NSAIDs, except aspirin, increase the risk of heart attack, heart failure, and stroke. These can be fatal. The risk is higher if you use more than directed or for longer than directed.

Sore throat warning:

Severe or persistent sore throat or sore throat accompanied by high fever, headache, nausea, and vomiting may be serious. Consult doctor promptly. Do not use more than 2 days or administer to children under 3 years of age unless directed by doctor.

Do not use

- if the child has ever had an allergic reaction to any other pain reliever/fever reducer
- right before or after heart surgery

Ask a doctor before use if

- stomach bleeding warning applies to the child
- child has problems or serious side effects from taking pain relievers or fever reducers
- child has a history of stomach problems, such as heartburn
- child has high blood pressure, heart disease, liver cirrhosis, kidney disease, asthma, or had a stroke
- child has not been drinking fluids
- child has lost a lot of fluid due to vomiting or diarrhea
- child is taking a diuretic

Ask a doctor or pharmacist before use if the child is

- under a doctor's care for any serious condition
- taking any other drug

When using this product

- take with food or milk if stomach upset occurs

Stop use and ask a doctor if

- child experiences any of the following signs of stomach bleeding:
  - feels faint
  - vomits blood
  - has bloody or black stools
  - has stomach pain that does not get better
- child has symptoms of heart problems or stroke:
  - chest pain
  - trouble breathing
  - weakness in one part or side of body
  - slurred speech
  - leg swelling
- child does not get any relief within first day (24 hours) of treatment
- fever or pain gets worse or lasts more than 3 days
- redness or swelling is present in the painful area
- any new symptoms appear

Keep out of reach of children

In case of overdose, get medical help or contact a Poison Control Center right away.

DIRECTIONS

- this product does not contain directions or complete warnings for adult use
- do not give more than directed
- find right dose on chart below. If possible, use weight to dose; otherwise use age.
- repeat dose every 6-8 hours, if needed
- do not use more than 4 times a day

Dosing Chart
Weight (lb) | Age (yr) | Dose (tablets)
under 48 lb | under 6 yr | ask a doctor
48-71 lb | 6-10 yr | 2 tablets
72-95 lb | 11 yr | 3 tablets

OTHER INFORMATION

- one dose lasts 6-8 hours
- store at 20-25°C (68-77°F)
- avoid excessive heat above 40°C (104°F)
- see side of box for lot number and expiration date

INACTIVE INGREDIENTS

acetylated monoglycerides, carnauba wax, colloidal silicon dioxide, corn starch, croscarmellose sodium, methylparaben, microcrystalline cellulose, pharmaceutical glaze, pharmaceutical ink, povidone, pregelatinized starch, propylparaben, sodium benzoate, stearic acid, sucrose, synthetic iron oxides, titanium dioxide

QUESTIONS OR COMMENTS?

call toll free 1-800-88-ADVIL or ask your pharmacist, doctor or health care professional

PRINCIPAL DISPLAY PANEL

Junior Strength
Advil®

Ibuprofen Tablets, 100 mg
Pain Reliever/Fever Reducer (NSAID)

Fever
Aches & Pains

Lasts Up To
8
Hours

for ages 6-11 years

24 COATED
TABLETS